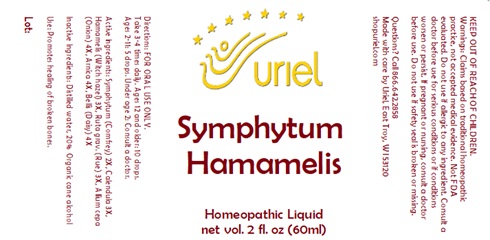 DRUG LABEL: Symphytum Hamamelis
NDC: 48951-8222 | Form: LIQUID
Manufacturer: Uriel Pharmacy Inc.
Category: homeopathic | Type: HUMAN OTC DRUG LABEL
Date: 20231128

ACTIVE INGREDIENTS: COMFREY ROOT 2 [hp_X]/1 mL; CALENDULA OFFICINALIS FLOWERING TOP 3 [hp_X]/1 mL; HAMAMELIS VIRGINIANA TOP 3 [hp_X]/1 mL; RUTA GRAVEOLENS FLOWERING TOP 3 [hp_X]/1 mL; ONION 4 [hp_X]/1 mL; ARNICA MONTANA 4 [hp_X]/1 mL; BELLIS PERENNIS 4 [hp_X]/1 mL
INACTIVE INGREDIENTS: WATER; ALCOHOL

Symphytum Hamamelis

INDICATIONS AND USAGE

Directions: FOR ORAL USE ONLY.

DOSAGE AND ADMINISTRATION

Take 3-4 times daily. Ages 12 and older: 10 drops. Ages 2-11: 5 drops. Under age 2: Consult a doctor.

ACTIVE INGREDIENT

Active Ingredients: Symphytum (Comfrey) 2X, Calendula 3X, Hamamelis (Witch hazel) 3X, Ruta grav. (Rue) 3X, Allium cepa (Onion) 4X, Arnica 4X, Bellis (Daisy) 4X

Inactive Ingredients: Distilled water, Organic cane alcohol

PURPOSE

Use: Promotes healing of broken bones.

KEEP OUT OF REACH OF CHILDREN.

WARNINGS

Warnings: Claims based on traditional homeopathic practice, not accepted medical evidence. Not FDA evaluated. Do not use if allergic to any ingredient. Consult a doctor before use for serious conditions or if conditions worsen or persist. If pregnant or nursing, consult a doctor before use. Do not use if safety seal is broken or missing.

QUESTIONS

Questions? Call 866.642.2858 Made with care by Uriel, East Troy, WI 53120 shopuriel.com